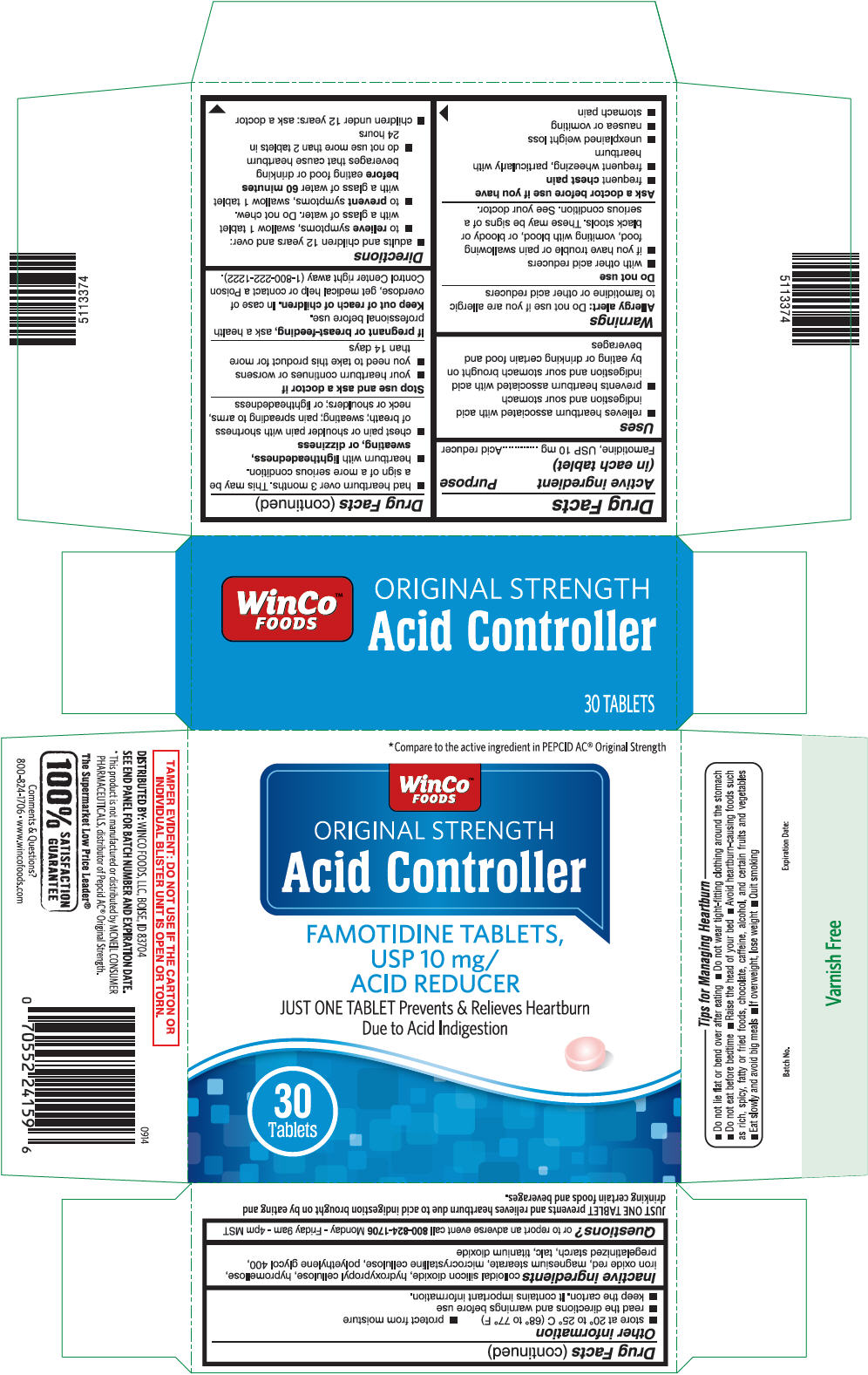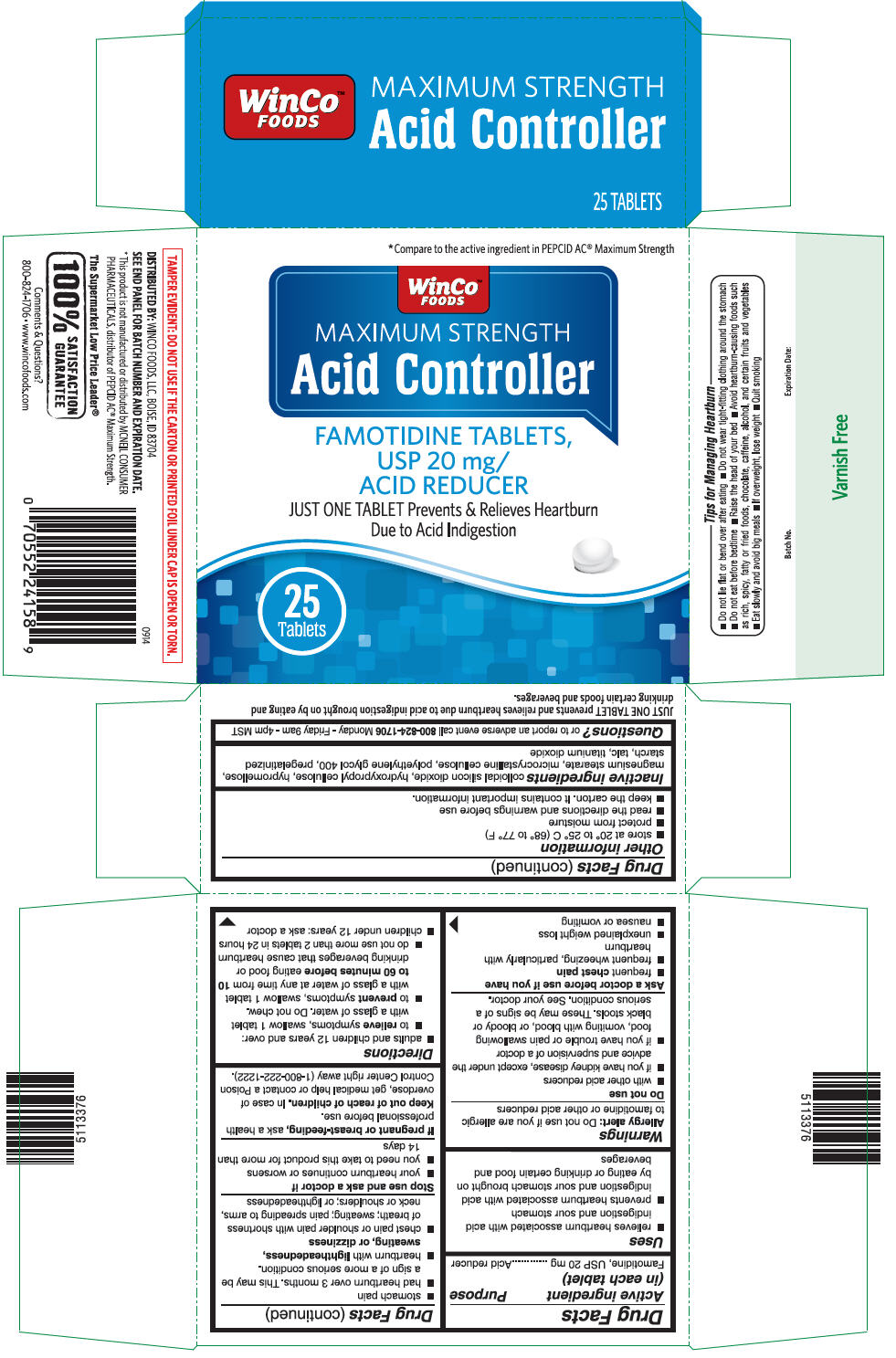 DRUG LABEL: Famotidine - Acid Controller
NDC: 67091-242 | Form: TABLET, FILM COATED
Manufacturer: WinCo Foods, LLC
Category: otc | Type: HUMAN OTC DRUG LABEL
Date: 20180912

ACTIVE INGREDIENTS: FAMOTIDINE 10 mg/1 1
INACTIVE INGREDIENTS: SILICON DIOXIDE; HYDROXYPROPYL CELLULOSE (1200000 MW); HYPROMELLOSE, UNSPECIFIED; FERRIC OXIDE RED; MAGNESIUM STEARATE; MICROCRYSTALLINE CELLULOSE; POLYETHYLENE GLYCOL 400; STARCH, CORN; TALC; TITANIUM DIOXIDE

Famotidine - Acid Controller

Drug Facts

Active ingredient (in each tablet)

Famotidine, USP 10 mg
Famotidine, USP 20 mg

Purpose

Acid reducer

Uses

- relieves heartburn associated with acid indigestion and sour stomach
- prevents heartburn associated with acid indigestion and sour stomach brought on by eating or drinking certain food and beverages

Warnings

Allergy alert

Do not use if you are allergic to famotidine or other acid reducers

Do not use

Famotidine USP, 10 mg

- with other acid reducers
- if you have trouble or pain swallowing food, vomiting with blood, or bloody or black stools. These may be signs of a serious condition. See your doctor.

Famotidine USP, 20 mg

- with other acid reducers
- if you have kidney disease, except under the advice and supervision of a doctor.
- if you have trouble or pain swallowing food, vomiting with blood, or bloody or black stools. These may be signs of a serious condition. See your doctor.

Ask a doctor before use if you have

- frequent chest pain
- frequent wheezing, particularly with heartburn
- unexplained weight loss
- nausea or vomiting
- stomach pain
- had heartburn over 3 months. This may be a sign of a more serious condition.
- heartburn with lightheadedness, sweating, or dizziness
- chest pain or shoulder pain with shortness of breath; sweating; pain spreading to arms, neck or shoulders; or lightheadedness

Stop use and ask a doctor if

- your heartburn continues or worsens
- you need to take this product for more than 14 days

PREGNANCY OR BREAST FEEDING

If pregnant or breast-feeding, ask a health professional before use.

Keep out of reach of children. In case of overdose, get medical help or contact a Poison Control Center right away (1-800-222-1222).

Directions

Famotidine USP, 10 mg

- adults and children 12 years and over:
  - to relieve symptoms, swallow 1 tablet with a glass of water. Do not chew.
  - to prevent symptoms, swallow 1 tablet with a glass of water 60 minutes before eating food or drinking beverages that cause heartburn
  - do not use more than 2 tablets in 24 hours
- children under 12 years: ask a doctor

Famotidine USP, 20 mg

- adults and children 12 years and over:
  - to relieve symptoms, swallow 1 tablet with a glass of water. Do not chew.
  - to prevent symptoms, swallow 1 tablet with a glass of water at any time from 10 to 60 minutes before eating food or drinking beverages that cause heartburn
  - do not use more than 2 tablets in 24 hours
- children under 12 years: ask a doctor

Other information

- store at 20° to 25° C (68° to 77° F)
- protect from moisture
- read the directions and warnings before use
- keep the carton. It contains important information.

Inactive ingredients

colloidal silicon dioxide, hydroxypropyl cellulose, hypromellose, iron oxide red (only for Famotidine USP, 10 mg), magnesium stearate, microcrystalline cellulose, polyethylene glycol 400, pregelatinized starch, talc, titanium dioxide

Questions?

or to report an adverse event call 800-824-1706 Monday - Friday 9am - 4pm MST

DISTRIBUTED BY: WINCO FOODS, LLC, BOISE, ID 83704

PRINCIPAL DISPLAY PANEL - 10 mg Blister Pack Carton

*Compare to the active ingredient in PEPCID AC® Original Strength

WinCo™
FOODS
ORIGINAL STRENGTH
Acid Controller

FAMOTIDINE TABLETS,
USP 10 mg/
ACID REDUCER
JUST ONE TABLET Prevents & Relieves Heartburn
Due to Acid Indigestion

30
Tablets

PRINCIPAL DISPLAY PANEL - 20 mg Blister Pack Carton

*Compare to the active ingredient in PEPCID AC® Maximum Strength

WinCo™
FOODS
MAXIMUM STRENGTH
Acid Controller

FAMOTIDINE TABLETS,
USP 20 mg/
ACID REDUCER
JUST ONE TABLET Prevents & Relieves Heartburn
Due to Acid Indigestion

25
Tablets